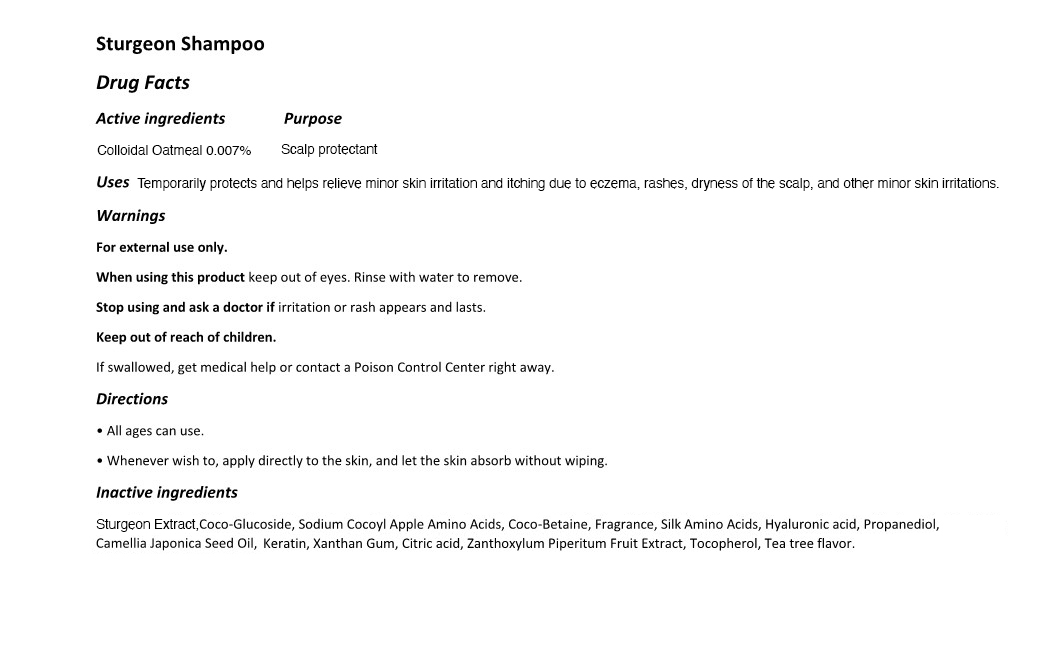 DRUG LABEL: THE ZOEUN SKIN TOTAL CARE
NDC: 83636-111 | Form: SHAMPOO
Manufacturer: Sturgeonbio Co.,Ltd.
Category: otc | Type: HUMAN OTC DRUG LABEL
Date: 20251001

ACTIVE INGREDIENTS: OATMEAL 0.007 g/100 mL
INACTIVE INGREDIENTS: CITRIC ACID MONOHYDRATE; TOCOPHEROL; MELALEUCA ALTERNIFOLIA (TEA TREE) LEAF OIL; XANTHAN GUM; FRAGRANCE CLEAN ORC0600327; STURGEON, UNSPECIFIED; PROPANEDIOL; TEA LEAF OIL; COCAMIDOPROPYL BETAINE; BUTYLENE GLYCOL; COCODIMONIUM HYDROXYPROPYL HYDROLYZED KERATIN (1000 MW); COCO GLUCOSIDE; CAPRYLYL/CAPRYL OLIGOGLUCOSIDE; SODIUM COCOYL APPLE AMINO ACIDS; ZANTHOXYLUM PIPERITUM FRUIT PULP

111 THE ZOEUN SKIN TOTAL CARE SHAMPOO

Active Ingredients

Colloidal Oatmeal 0.007%

Uses

Temporarily protects and helps relieve minor skin irritation and itching due to eczema, rashes, dryness of the scalp, and other minor skin irritations.

purpose

Scalp protectant

warnings

Keep out of reach of children.
If swallowed, get medical help or contact a Poison Control Center right away.

warnings

Stop using and ask a doctor if irritation or rash appears and lasts.

warnings

When using this product keep out of eyes. Rinse with water to remove.

warnings

For external use only.

directions

• All ages can use.
• Whenever wish to, apply directly to the skin, and let the skin absorb without wiping.

Inactive Indgredients

Sturgeon Extract, Coco-Glucoside, Sodium Cocoyl Apple Amino Acids, Coco-Betaine, Fragrance, Silk Amino Acids, Hyaluronic acid, Propanediol, Camellia Japonica Seed Oil,
Keratin, Xanthan Gum, Citric acid, Zanthoxylum Piperitum Fruit Extract, Tocopherol, Tea tree flavor.